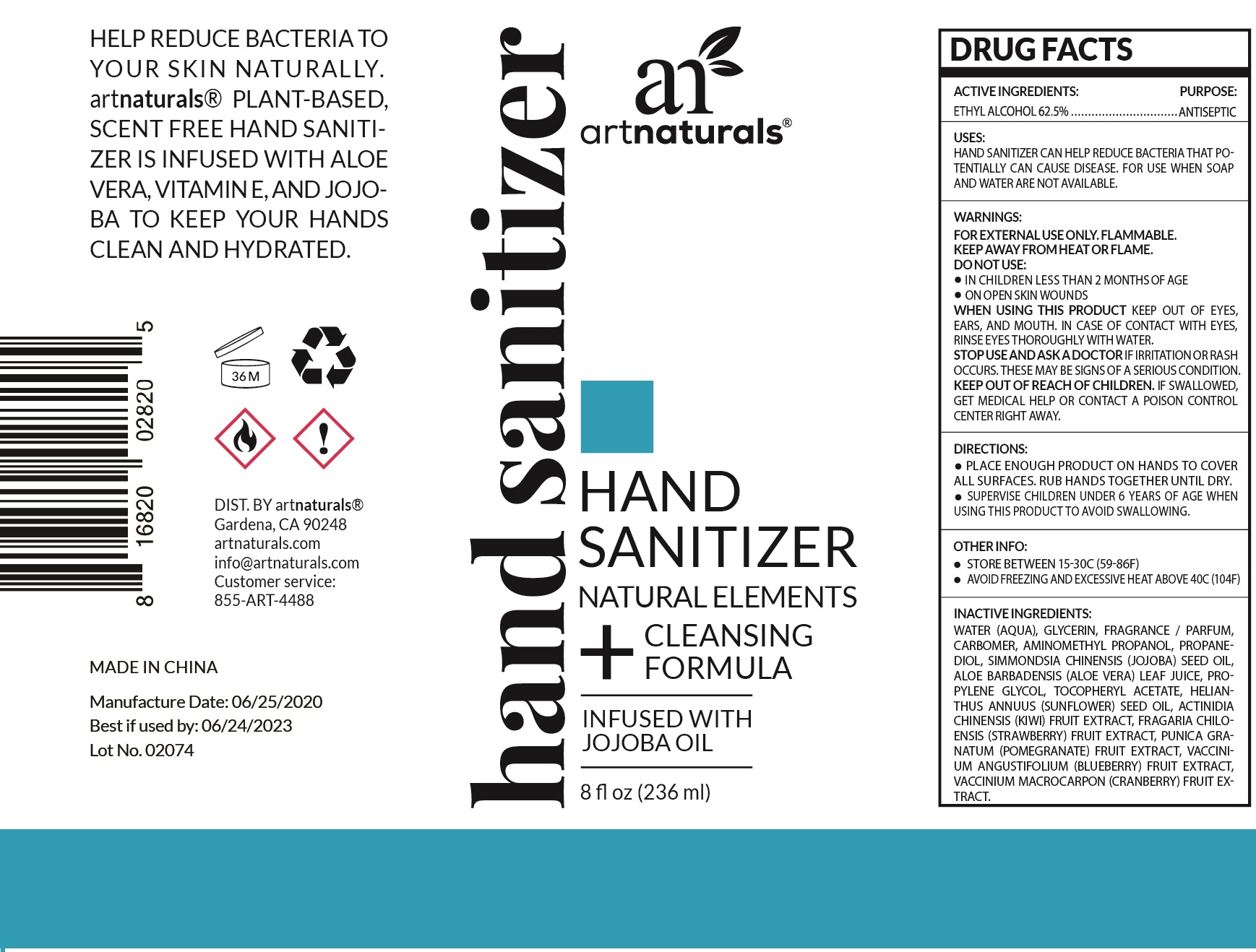 DRUG LABEL: Artnaturals Hand Sanitizer
NDC: 78706-018 | Form: GEL
Manufacturer: VIRGIN SCENT INC.
Category: otc | Type: HUMAN OTC DRUG LABEL
Date: 20200629

ACTIVE INGREDIENTS: ALCOHOL 0.625 mL/1 mL
INACTIVE INGREDIENTS: WATER; GLYCERIN; CARBOMER HOMOPOLYMER, UNSPECIFIED TYPE; AMINOMETHYLPROPANOL; PROPANEDIOL; JOJOBA OIL; ALOE VERA LEAF; PROPYLENE GLYCOL; .ALPHA.-TOCOPHEROL ACETATE; SUNFLOWER OIL; KIWI FRUIT; STRAWBERRY; POMEGRANATE; LOWBUSH BLUEBERRY; CRANBERRY

Artnaturals Hand Sanitizer

ACTIVE INGREDIENTS:

ETHYL ALCOHOL 62.5%

PURPOSE:

ANTISEPTIC

USES:

HAND SANITIZER CAN HELP REDUCE BACTERIA THAT POTENTIALLY CAN CAUSE DISEASE. FOR USE WHEN SOAP AND WATER ARE NOT AVAILABLE.

WARNINGS:

FOR EXTERNAL USE ONLY. FLAMMABLE.

KEEP AWAY FROM HEAT OR FLAME

DO NOT USE:

- IN CHILDREN LESS THAN 2 MONTHS OF AGE
- ON OPEN SKIN WOUNDS

WHEN USING THIS PRODUCT

KEEP OUT OF EYES, EARS, AND MOUTH. IN CASE OF CONTACT WITH EYES, RINSE EYES THOROUGHLY WITH WATER.

STOP USE AND ASK A DOCTOR

IF IRRITATION OR RASH OCCURS. THESE MAY BE SIGNS OF A SERIOUS CONDITION.

KEEP OUT OF REACH OF CHILDREN.

IF SWALLOWED, GET MEDICAL HELP OR CONTACT A POISON CONTROL CENTER RIGHT AWAY.

DIRECTIONS:

- PLACE ENOUGH PRODUCT ON HANDS TO COVER ALL SURFACES. RUB HANDS TOGETHER UNTIL DRY.
- SUPERVISE CHILDREN UNDER 6 YEARS OF AGE WHEN USING THIS PRODUCT TO AVOID SWALLOWING.

OTHER INFO:

- STORE BETWEEN 15-30C (59-86F)
- AVOID FREEZING AND EXCESSIVE HEAT ABOVE 40C (104F)

INACTIVE INGREDIENTS:

WATER (AQUA), GLYCERIN, FRAGRANCE / PARFUM, CARBOMER, AMINOMETHYL PROPANOL, PROPANEDIOL, SIMMONDSIA CHINENSIS (JOJOBA) SEED OIL, ALOE BARBADENSIS (ALOE VERA) LEAF JUICE, PROPYLENE GLYCOL, TOCOPHERYL ACETATE, HELIANTHUS ANNUUS (SUNFLOWER) SEED OIL, ACTINIDIA CHINENSIS (KIWI) FRUIT EXTRACT, FRAGARIA CHILOENSIS (STRAWBERRY) FRUIT EXTRACT, PUNICA GRANATUM (POMEGRANATE)FRUIT EXTRACT, VACCINIUM ANGUSTIFOLIUM (BLUEBERRY) FRUIT EXTRACT, VACCINUM MACROCARPON (CRANBERRY) FRUIT EXTRACT.